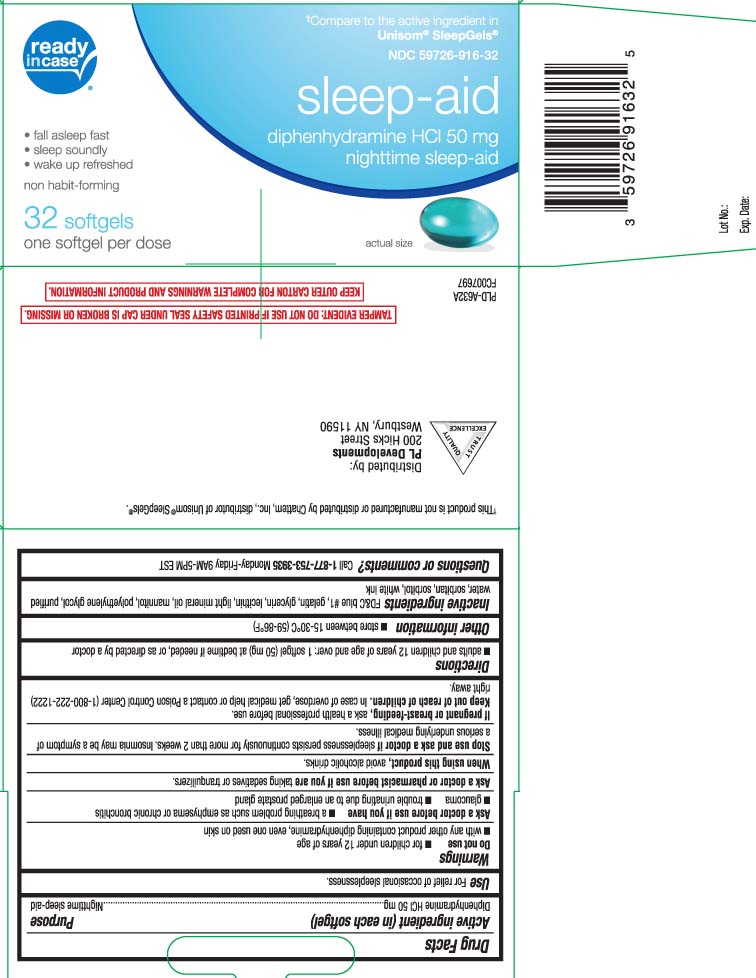 DRUG LABEL: Nighttime Sleep Aid
NDC: 59726-916 | Form: CAPSULE
Manufacturer: P & L Development, LLC
Category: otc | Type: HUMAN OTC DRUG LABEL
Date: 20260210

ACTIVE INGREDIENTS: DIPHENHYDRAMINE HYDROCHLORIDE 50 mg/1 1
INACTIVE INGREDIENTS: FD&C BLUE NO. 1; GELATIN; GLYCERIN; LECITHIN, SOYBEAN; POLYETHYLENE GLYCOL, UNSPECIFIED; WATER; SORBITAN; SORBITOL; LIGHT MINERAL OIL; MANNITOL

Drug Facts

Active ingredient (in each softgel)

Diphenhydramine HCl 50 mg

Purpose

Nighttime sleep-aid

Use

for relief of occasional sleeplessness.

Warnings

Do not use

- for children under 12 years of age
- with any other product containing diphenhydramine, even one used on skin

Ask a doctor before use if you have

- a breathing problem such as emphysema or chronic bronchitis
- glaucoma
- trouble urinating due to an enlarged prostate gland

Ask a doctor or pharmacist before use if you are

taking sedatives or tranquilizers.

When using this product

avoid alcoholic drinks.

Stop use and ask a doctor if

sleeplessness persists continuously for more than 2 weeks. Insomnia may be a symptom of a serious underlying medical illness.

If pregnant or breast-feeding,

ask a health professional before use.

Keep out of reach of children.

In case of overdose, get medical help or contact a Poison Control Center (1-800-222-1222) right away.

Directions

- adults and children 12 years of age and over: 1 softgel (50 mg) at bedtime if needed, or as directed by a doctor

Other information

- store between 15-30°C (59-86°F)

Inactive ingredients

FD&C blue #1, gelatin, glycerin, lecithin, light mineral oil, mannitol, polyethylene glycol, purified water, sorbitol sorbitan, white ink

Questions or comments?

Call 1-877-753-3935 Monday-Friday 9AM-5PM EST

Principal Display Panel

†Compare to the active ingredient in Unisom® SleepGels®

Sleep Aid

Diphenhydramine HCl, 50 mg

Nighttime Sleep-Aid

- Fall Asleep Fast
- Sleep Soundly
- Wake Up Refreshed

non-habit-forming

softgels

One Softgel Per Dose

†This product is not manufactured or distributed by Chattem, Inc., distributor of Unisom® SleepGels®.

TAMPER EVIDENT: DO NOT USE IF PRINTED SAFETY SEAL UNDER CAP IS BROKEN OR MISSING.

KEEP OUTER CARTON FOR COMPLETE WARNINGS AND PRODUCT INFORMATION.

Distributed by:

PL Developments

200 Hicks Street

Westbury, NY 11590

Package Label

READYinCASE Sleep Aid